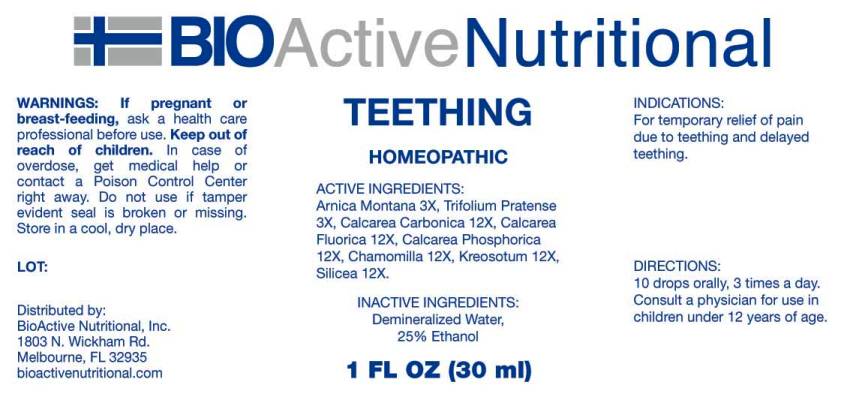 DRUG LABEL: Teething
NDC: 43857-0406 | Form: LIQUID
Manufacturer: BioActive Nutritional, Inc.
Category: homeopathic | Type: HUMAN OTC DRUG LABEL
Date: 20160727

ACTIVE INGREDIENTS: ARNICA MONTANA 3 [hp_X]/1 mL; TRIFOLIUM PRATENSE FLOWER 3 [hp_X]/1 mL; OYSTER SHELL CALCIUM CARBONATE, CRUDE 12 [hp_X]/1 mL; CALCIUM FLUORIDE 12 [hp_X]/1 mL; TRIBASIC CALCIUM PHOSPHATE 12 [hp_X]/1 mL; MATRICARIA RECUTITA 12 [hp_X]/1 mL; WOOD CREOSOTE 12 [hp_X]/1 mL; SILICON DIOXIDE 12 [hp_X]/1 mL
INACTIVE INGREDIENTS: WATER; ALCOHOL

Drug Facts:

ACTIVE INGREDIENTS:

Arnica Montana 3X, Trifolium Pratense 3X, Calcarea Carbonica 12X, Calcarea Fluorica 12X, Calcarea Phosphorica 12X, Chamomilla 12X, Kreosotum 12X, Silicea 12X

INDICATIONS:

For temporary relief of pain due to teething and delayed teething.

WARNINGS:

If pregnant or breast-feeding, ask a health care professional before use.

Keep out of reach of children. In case of overdose, get medical help or contact a Poison Control Center right away.

Do not use if tamper evident seal is broken or missing.

Store in cool, dry place.

Keep out of reach of children. In case of overdose, get medical help or contact a Poison Control Center right away.

DIRECTIONS:

10 drops orally, 3 times a day. Consult a physician for use in children under 12 years of age.

INDICATIONS:

For temporary relief of pain due to teething and delayed teething.

INACTIVE INGREDIENTS:

Demineralized water, 25% Ethanol

QUESTIONS:

Distributed by:
BioActive Nutritional, Inc.
1803 N. Wickham Rd.
Melbourne, FL 32935
bioactivenutritional.com

PACKAGE LABEL DISPLAY:

BIOActive Nutritional

TEETHING

HOMEOPATHIC

1 FL OZ (30 ml)